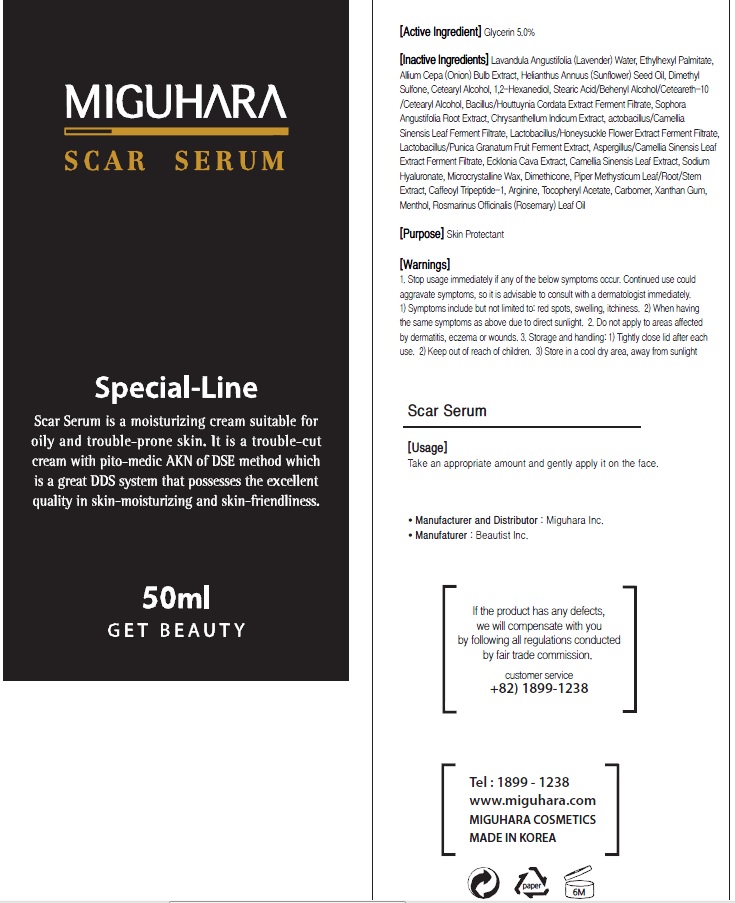 DRUG LABEL: Scar Serum
NDC: 70380-310 | Form: CREAM
Manufacturer: MIGUHARA
Category: otc | Type: HUMAN OTC DRUG LABEL
Date: 20160224

ACTIVE INGREDIENTS: Glycerin 2.5 g/50 mL
INACTIVE INGREDIENTS: LAVANDULA ANGUSTIFOLIA FLOWER; Ethylhexyl Palmitate

ACTIVE INGREDIENT

Active Ingredient: Glycerin 5.0%

INACTIVE INGREDIENT

Inactive Ingredients: Lavandula Angustifolia (Lavender) Water, Ethylhexyl Palmitate, Allium Cepa (Onion) Bulb Extract, Helianthus Annuus (Sunflower) Seed Oil, Dimethyl Sulfone, Cetearyl Alcohol, 1,2-Hexanediol, Stearic Acid/Behenyl Alcohol/Ceteareth-10/Cetearyl Alcohol, Bacillus/Houttuynia Cordata Extract Ferment Filtrate, Sophora Angustifolia Root Extract, Chrysanthellum Indicum Extract, actobacillus/Camellia Sinensis Leaf Ferment Filtrate, Lactobacillus/Honeysuckle Flower Extract Ferment Filtrate, Lactobacillus/Punica Granatum Fruit Ferment Extract, Aspergillus/Camellia Sinensis Leaf Extract Ferment Filtrate, Ecklonia Cava Extract, Camellia Sinensis Leaf Extract, Sodium Hyaluronate, Microcrystalline Wax, Dimethicone, Piper Methysticum Leaf/Root/Stem Extract, Caffeoyl Tripeptide-1, Arginine, Tocopheryl Acetate, Carbomer, Xanthan Gum, Menthol, Rosmarinus Officinalis (Rosemary) Leaf Oil

PURPOSE

Purpose: Skin Protectant

WARNINGS

1. Stop usage immediately if any of the below symptoms occur. Continued use could aggravate symptoms, so it is advisable to consult with a dermatologist immediately. 1) Symptoms include but not limited to: red spots, swelling, itchiness. 2) When having the same symptoms as above due to direct sunlight. 2. Do not apply to areas affected by dermatitis, eczema or wounds. 3. Storage and handling: 1) Tightly close lid after each use. 2 Keep out of reach of children 3) Store in a cool dry area, away from sunlight

KEEP OUT OF REACH OF CHILDREN

Usage

Usage: Take an appropriate amount and gently apply it on the face

Usage

Usage: Take an appropriate amount and gently apply it on the face